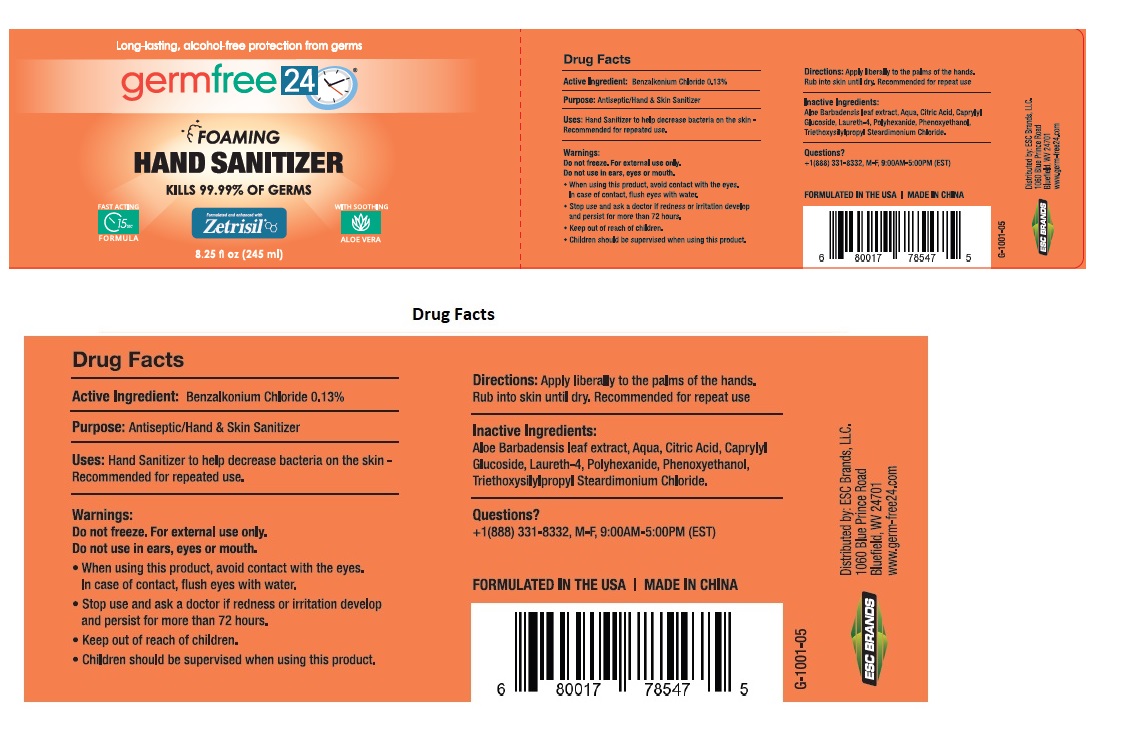 DRUG LABEL: Germ Free 24 Hand Sanitizer
NDC: 71884-006 | Form: LIQUID
Manufacturer: Enviro Specialty Chemicals Inc
Category: otc | Type: HUMAN OTC DRUG LABEL
Date: 20241231

ACTIVE INGREDIENTS: BENZALKONIUM CHLORIDE 1.3 mg/1 mL
INACTIVE INGREDIENTS: ALOE VERA LEAF; WATER; CITRIC ACID MONOHYDRATE; CAPRYLYL GLUCOSIDE; LAURETH-4; POLIHEXANIDE; PHENOXYETHANOL; TRIETHOXYSILYLPROPYL STEARDIMONIUM CHLORIDE

germfree 24® FOAMING HAND SANITIZER

Active Ingredient:

Benzalkonium Chloride 0.13%

Purpose:

Antiseptic/Hand & Skin Sanitizer

Uses:

Hand Sanitizer to help decrease bacteria on the skin - Recommended for repeated use.

Warnings:

Do not freeze. For external use only.

Do not use in ears, eyes or mouth.

• When using this product, avoid contact with the eyes. In case of contact, flush eyes with water.

• Stop use and ask a doctor if redness or irritation develop and persist for more than 72 hours.

• Keep out of reach of children.

• Children should be supervised when using this product.

Directions:

Apply liberally to the palms of the hands. Rub into skin until dry. Recommended for repeat use.

Inactive Ingredients:

Aloe Barbadensis leaf extract, Aqua, Citric Acid, Caprylyl Glucoside, Laureth-4, Polyhexanide, Phenoxyethanol, Triethoxysilylpropyl Steardimonium Chloride.

Questions?

+1(888) 331-8332, M-F, 9:00AM-5:00PM (EST)

Long-lasting, alcohol-free protection from germs

FOAMING HAND SANITIZER

KILLS 99.99% OF GERMS

Formulated and enhanced with Zetrisil®

FAST ACTING 15 SEC FORMULA

WITH SOOTHING ALOE VERA

FORMULATED IN THE USA

MADE IN CHINA

Distributed by: ESC Brands, LLC.
1060 Blue Prince Road
Bluefield, WV 24701
www.germ-free24.com